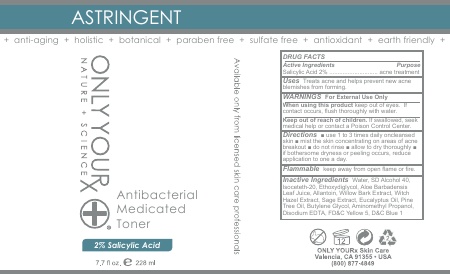 DRUG LABEL: Antibacterial Medicated Toner -2% Salicylic Acid
NDC: 70367-011 | Form: SPRAY
Manufacturer: Only Yourx, Inc.
Category: otc | Type: HUMAN OTC DRUG LABEL
Date: 20200123

ACTIVE INGREDIENTS: SALICYLIC ACID 2 g/100 mL
INACTIVE INGREDIENTS: WITCH HAZEL; PINE NEEDLE OIL (PINUS SYLVESTRIS); BUTYLENE GLYCOL; EUCALYPTUS OIL; MAGNESIUM DISODIUM EDTA; FD&C YELLOW NO. 5; FD&C BLUE NO. 1; AMINOMETHYL PROPANEDIOL; SAGE OIL; WATER; WILLOW BARK; ALOE ARBORESCENS LEAF; ISOCETETH-20; ETHOXYDIGLYCOL BEHENATE; ALLANTOIN

Warnings: For External Use Only

ACTIVE INGREDIENT

Salicylic Acid - 2%

PURPOSE

Acne Treatment

Uses

Treats acne and helps prevent new acne blemishes from forming

When using this product keep out of eyes. If contact occurs, flush thoroughly with water

Keep out of reach of children. if swallowed, seek medical help or contact a Poison Control Center

Directions:

use 1 to 3 times daily on cleansed skin. mist the skin concentratikng on areas of acne breakout. do not rinse. allow to dry thoroughly. if bothersome dryness or peeling occurs, reduce application to once a day.

Inactive Ingredients:

Water, SD Alcohol 40, Isoceteth-20, Ethoxydiglycol, Aloe Leaf Juice, Allantoin, Willow Bark Extract, Witch Hazel Extract, Sage Extract, Eucalyptus Oil, Pine Tree Oil, Butylene Glycol, Aminomethyl Propanol, Disodium EDTA, FD&C Yellow 5, FD&C Blue 1